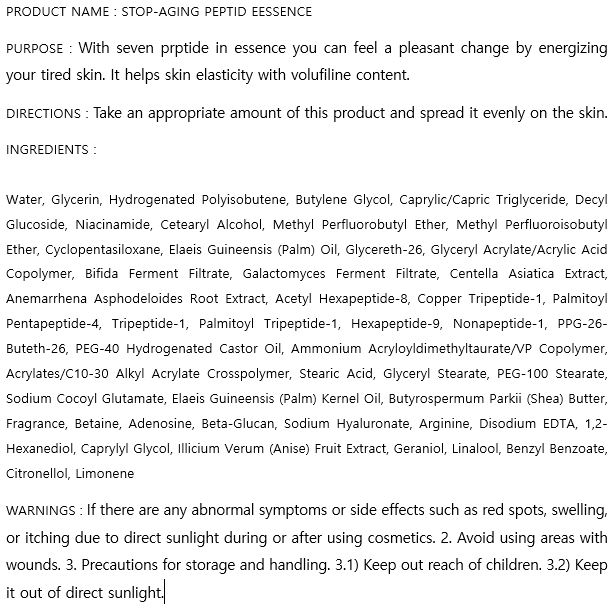 DRUG LABEL: STOP-AGING PEPTIDE ESSENCE
NDC: 74997-0006 | Form: CREAM
Manufacturer: J&J COMPANY
Category: otc | Type: HUMAN OTC DRUG LABEL
Date: 20200812

ACTIVE INGREDIENTS: NIACINAMIDE 2 g/100 mL; ADENOSINE 0.04 g/100 mL
INACTIVE INGREDIENTS: GLYCERIN; BUTYLENE GLYCOL; WATER

J&J COMPANY - STOP-AGING PEPTIDE ESSENCE

ACTIVE INGREDIENT

Niacinamide, Adenosine

INACTIVE INGREDIENT

Water, Glycerin, Hydrogenated Polyisobutene, Butylene Glycol, Caprylic/Capric Triglyceride, Decyl Glucoside, Niacinamide, Cetearyl Alcohol, Methyl Perfluorobutyl Ether, Methyl Perfluoroisobutyl Ether, Cyclopentasiloxane, Elaeis Guineensis (Palm) Oil, Glycereth-26, Glyceryl Acrylate/Acrylic Acid Copolymer, Bifida Ferment Filtrate, Galactomyces Ferment Filtrate, Centella Asiatica Extract, Anemarrhena Asphodeloides Root Extract, Acetyl Hexapeptide-8, Copper Tripeptide-1, Palmitoyl Pentapeptide-4, Tripeptide-1, Palmitoyl Tripeptide-1, Hexapeptide-9, Nonapeptide-1, PPG-26-Buteth-26, PEG-40 Hydrogenated Castor Oil, Ammonium Acryloyldimethyltaurate/VP Copolymer, Acrylates/C10-30 Alkyl Acrylate Crosspolymer, Stearic Acid, Glyceryl Stearate, PEG-100 Stearate, Sodium Cocoyl Glutamate, Elaeis Guineensis (Palm) Kernel Oil, Butyrospermum Parkii (Shea) Butter, Fragrance, Betaine, Adenosine, Beta-Glucan, Sodium Hyaluronate, Arginine, Disodium EDTA, 1,2-Hexanediol, Caprylyl Glycol, Illicium Verum (Anise) Fruit Extract, Geraniol, Linalool, Benzyl Benzoate, Citronellol, Limonene

PURPOSE

With seven peptide in eye cream user can feel a pleasant change by energizing your tired skin. It helps skin elasticity with volufiline content.

keep out of reach of the children

INDICATIONS AND USAGE

Take an appropriate amount of this product and spread it evenly on the skin.

WARNINGS

If there are any abnormal symptoms or side effects such as red spots, swelling, or itching due to direct sunlight during or after using cosmetics. 2. Avoid using areas with wounds. 3. Precautions for storage and handling. 3.1) Keep out reach of children. 3.2) Keep it out of direct sunlight.

DOSAGE AND ADMINISTRATION

for external use only